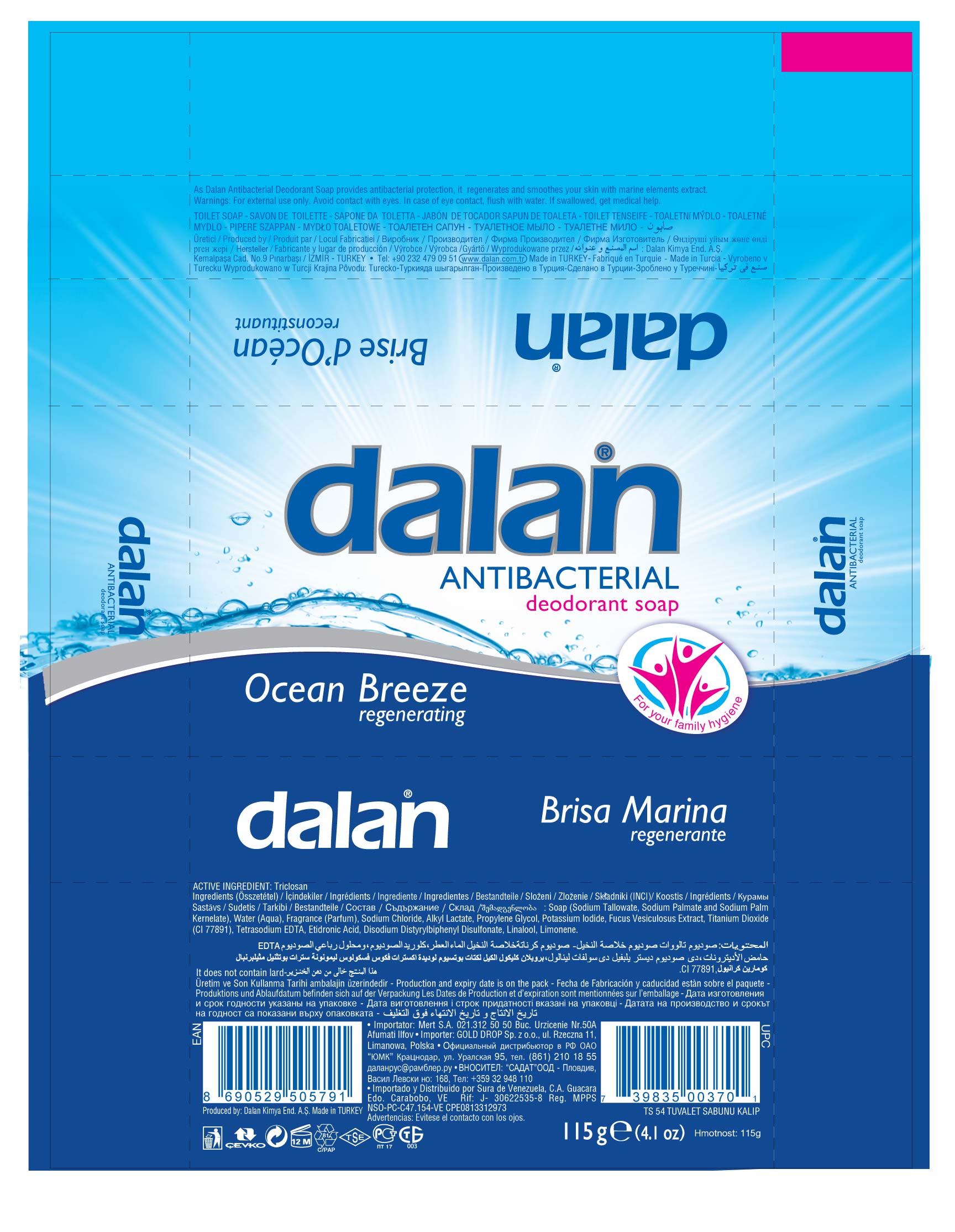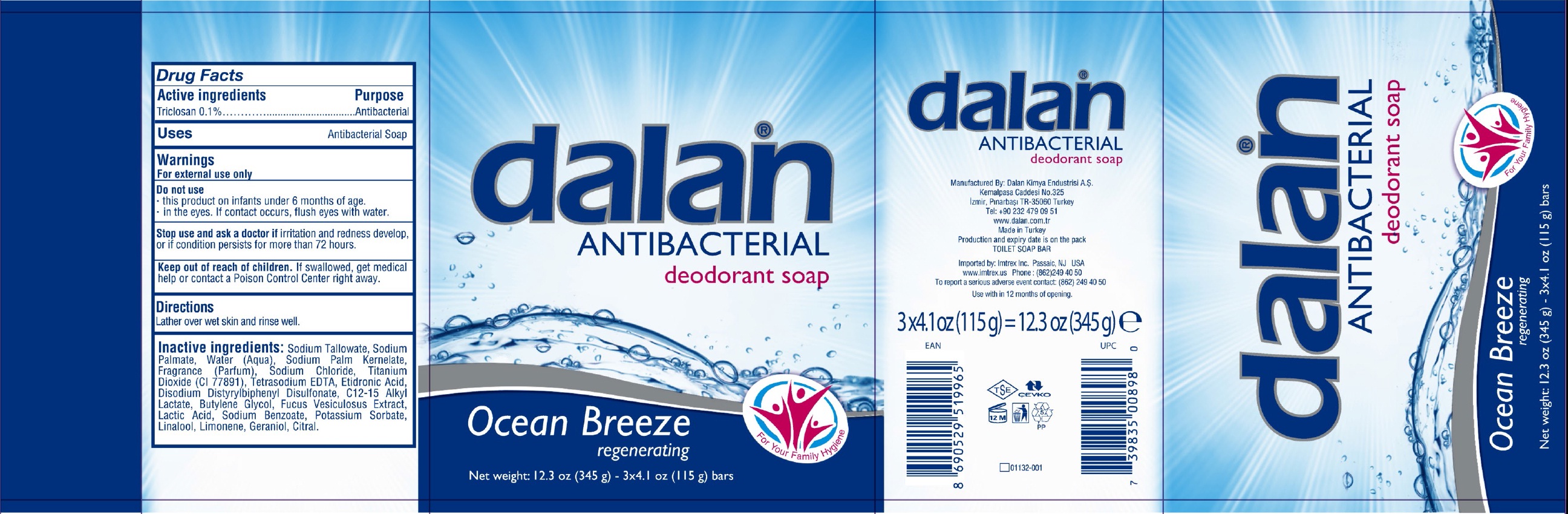 DRUG LABEL: Dalan Antibacterial Deodorant Ocean Breeze
NDC: 51209-010 | Form: SOAP
Manufacturer: Dalan Kimya Endustri A.S.
Category: otc | Type: HUMAN OTC DRUG LABEL
Date: 20160212

ACTIVE INGREDIENTS: TRICLOSAN 1 mg/1 g
INACTIVE INGREDIENTS: SODIUM PALMATE; WATER; SODIUM PALM KERNELATE; SODIUM CHLORIDE; TITANIUM DIOXIDE; EDETATE SODIUM; ETIDRONIC ACID; DISODIUM DISTYRYLBIPHENYL DISULFONATE; C12-15 ALKYL LACTATE; BUTYLENE GLYCOL; FUCUS VESICULOSUS; SODIUM BENZOATE; POTASSIUM SORBATE; LINALOOL, (+/-)-; GERANIOL; CITRAL

Dalan Antibacterial Deodorant Soap Ocean Breeze

Active ingredients

Triclosan 0.1%

Purpose

Antibacterial Soap

Uses

Antibacterial Soap

Warnings

For external use only

Do not use

- this product on infants under 6 months of age.
- in the eyes. If contact occurs, flush eyes with water.

Stop use and ask a doctor if

irritation and redness develop, or if condition persists for more than 72 hours.

Keep out of reach of children.

If swallowed, get medical help or contact a Poison Control Center right away.

Directions

Lather over wet skin and rinse well.

Inactive ingredients:

Sodium Tallowate, Sodium Palmate, Water (Aqua), Sodium Palm Kernelate, Fragrance (Parfum), Sodium Chloride, Titanium Dioxide (CI 77891), Tetrasodium EDTA, Etidronic Acid, Disodium Distyrylbiphenyl Disulfonate, C12-15 Alkyl Lactate, Butylene Glycol, Fucus Vesiculosus Extract, Lactice Acid, Sodium Benzoate, Potassium Sorbate, Linalool, Limonene, Geraniol, Citral.